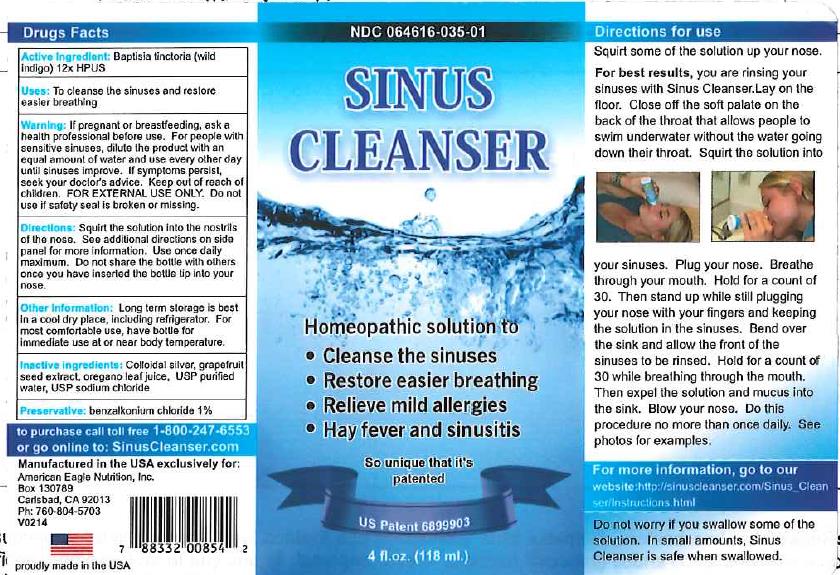 DRUG LABEL: Sinus Cleanser
NDC: 64616-035 | Form: LIQUID
Manufacturer: Vitality Works, Inc.
Category: homeopathic | Type: HUMAN OTC DRUG LABEL
Date: 20211230

ACTIVE INGREDIENTS: BAPTISIA TINCTORIA ROOT 12 1/1 mL
INACTIVE INGREDIENTS: OREGANO; CITRUS PARADISI SEED; SILVER; SODIUM CHLORIDE; WATER

Sinus Cleanser

Sinus Cleanser

Baptisia tinctoria 12X

Sinus Cleanser

Colloidal silver, grapefruit seed extract, oregano leaf juice, USP purified water, USP sodium chloride

Sinus Cleanser

If pregnant or breast feeding, ask a health professional before use. For people with sensitive sinuses, dilute the product with an equal amount of water and use every other day until sinuses improve. If symptoms persist, seek your doctor's advice. Keep out of reach of children. FOR EXTERNAL USE ONLY. Do not use if safety seal is broken.

Sinus Cleanser

Keep out of reach of children.

Sinus Cleanser

To cleanse the sinuses and restore easier breathing.

Sinus Cleanser

Squirt the solution into the nostrils of the nose. Use once daily maximum. Do not share the bottle with others once you have inserted the bottle tip in your nose.

Sinus Cleanser

To cleanse the sinuses and restore easier breathing.